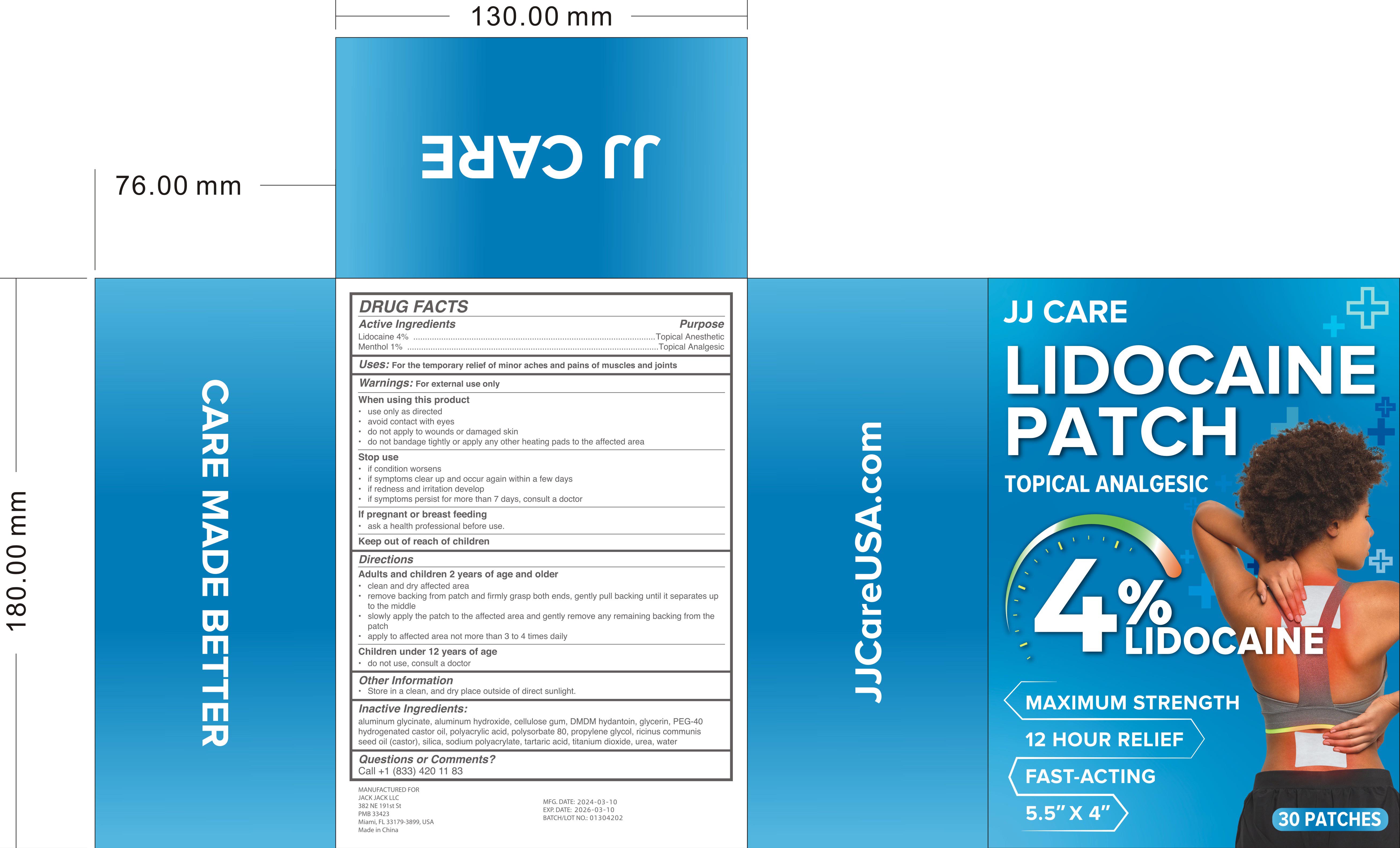 DRUG LABEL: Lidocaine Patch
NDC: 84273-002 | Form: PATCH
Manufacturer: Hunan En Pu Pharmaceutical Co., Ltd.
Category: otc | Type: HUMAN OTC DRUG LABEL
Date: 20240422

ACTIVE INGREDIENTS: LIDOCAINE 4 g/100 1; MENTHOL 1 g/100 1
INACTIVE INGREDIENTS: CASTOR OIL; TARTARIC ACID; POLYACRYLIC ACID (250000 MW); UREA; WATER; SILICON DIOXIDE; SODIUM POLYACRYLATE (2500000 MW); DIHYDROXYALUMINUM AMINOACETATE ANHYDROUS; POLYOXYL 40 HYDROGENATED CASTOR OIL; TITANIUM DIOXIDE; ALUMINUM HYDROXIDE; DMDM HYDANTOIN; CARBOXYMETHYLCELLULOSE; GLYCERIN; POLYSORBATE 80; PROPYLENE GLYCOL

Lidocaine Patch

Lidocaine Patch

ACTIVE INGREDIENT

Lidocaine 4%
Menthol 1%

PURPOSE

Topical Anesthetic

INDICATIONS AND USAGE

For the temporary relief of minor aches and pains of muscles and joints

WARNINGS

For external use only

use only as directed
avoid contact with eyes
do not apply to wounds or damaged skin
do not bandage tightly or apply any other heating pads to the affected area

WHEN USING

use only as directed
avoid contact with eyes
do not apply to wounds or damaged skin
do not bandage tightly or apply any other heating pads to the affected area

STOP USE

if condition worsens
if symptoms clear up and occur again within a few days
if redness and irritation develop
if symptoms persist for more than 7 days, consult a doctor

Keep out of reach of children

DOSAGE AND ADMINISTRATION

Adults and children 2 years of age and older
clean and dry affected area
remove backing trom patch and firmly grasp both ends, gently pull backing until it separates up to the middle
slowly apply the patch to the affected area and gently remove any remaining backing from the patch
apply to affected area not more than 3 to 4 times daily

STORAGE AND HANDLING

Store in a clean, and dry place outside of direct sunlight.

INACTIVE INGREDIENT

Aluminum Glycinate
Aluminum Hydroxide
Cellulose Gum
DMDM hydantoin
Glycerin
PEG-40 Hydrogenated Castor Oil
Polyacrylic Acid
Polysorbate 80
Propylene Glycol
Ricinus Communis Seed Oil (Castor)
Silica
Sodium Polyacrylate
Tartaric Acid
Titanium Dioxide
Urea
Water